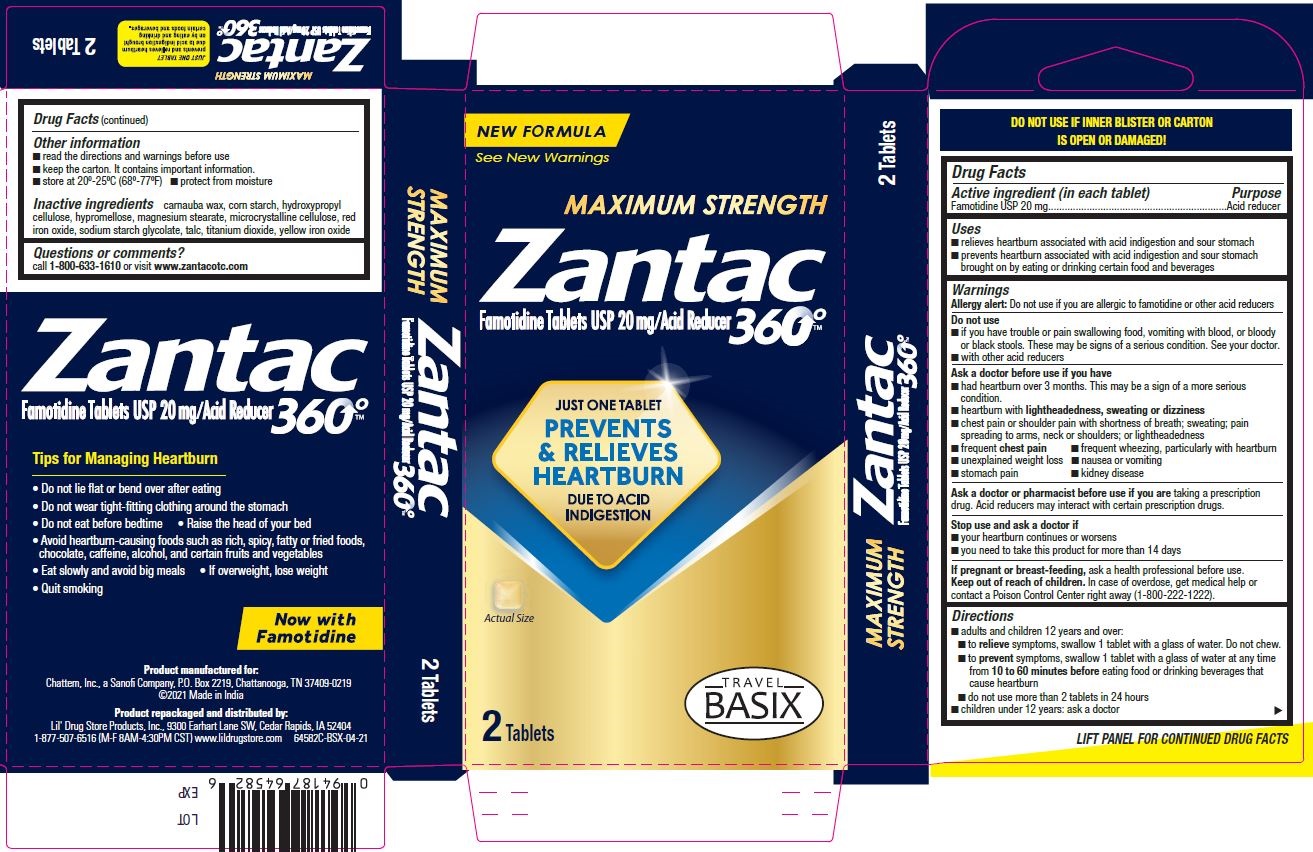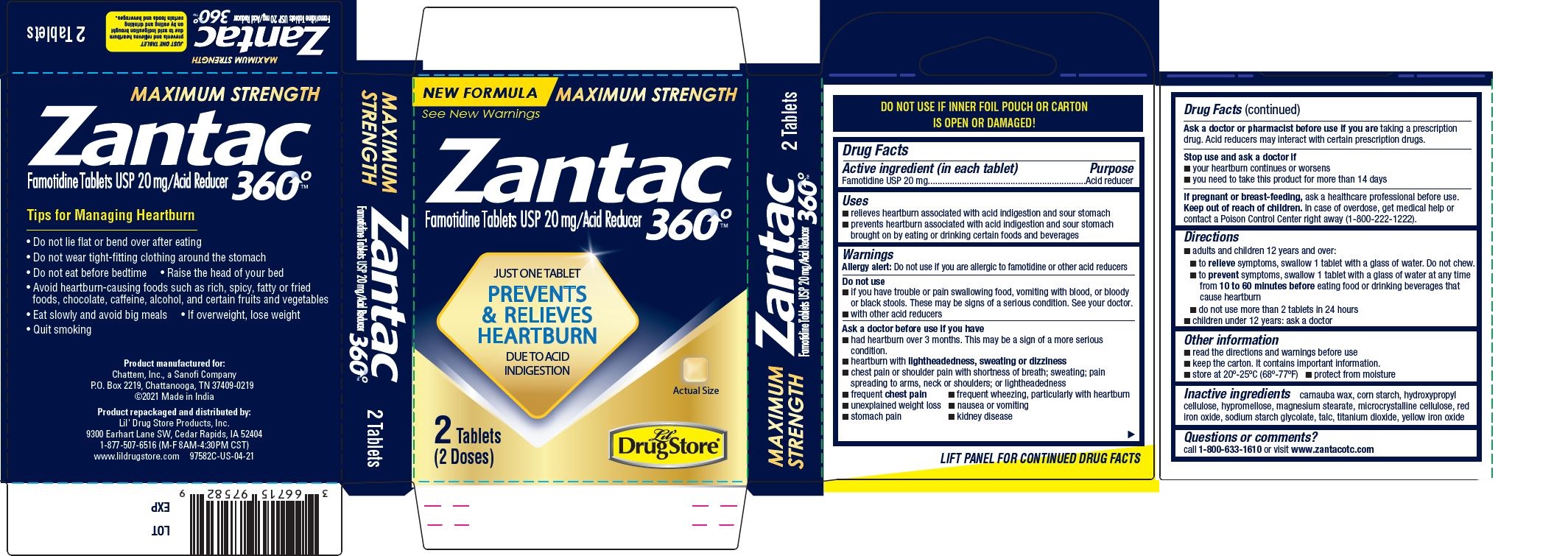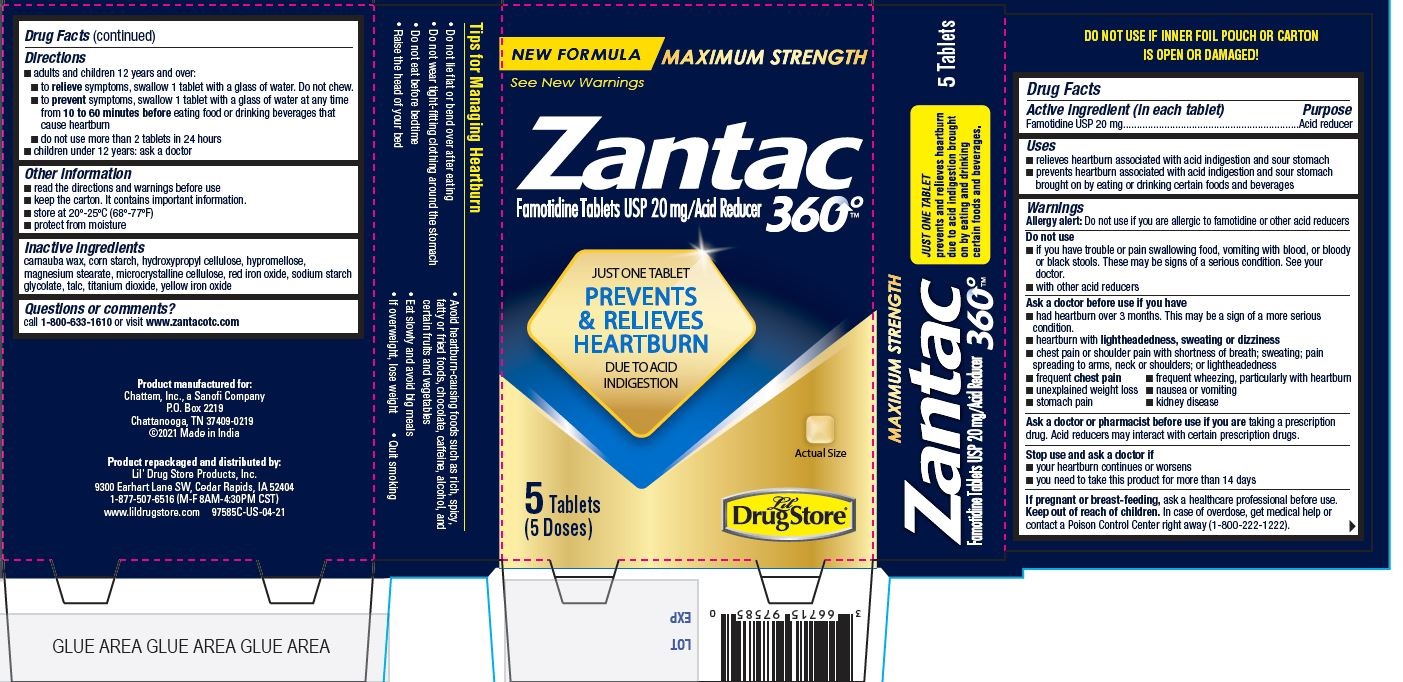 DRUG LABEL: Zantac 360
NDC: 66715-9758 | Form: TABLET, FILM COATED
Manufacturer: Lil' Drug Store Products, Inc
Category: otc | Type: HUMAN OTC DRUG LABEL
Date: 20241119

ACTIVE INGREDIENTS: FAMOTIDINE 20 mg/1 1
INACTIVE INGREDIENTS: MAGNESIUM STEARATE; TALC; FERRIC OXIDE YELLOW; HYPROMELLOSE 2910 (5 MPA.S); SODIUM STARCH GLYCOLATE TYPE A CORN; CARNAUBA WAX; CELLULOSE, MICROCRYSTALLINE; HYDROXYPROPYL CELLULOSE (1600000 WAMW); STARCH, CORN; TITANIUM DIOXIDE; FERRIC OXIDE RED

Zantac 360°™, Lil Drug Store, Zantac 360°™, Travel BASIX

Active Ingredient

Active ingredient (in each tablet)
Famotidine USP 20 mg

Purpose

Acid reducer

Uses

- relieves heartburn associated with acid indigestion and sour stomach
- prevents heartburn associated with acid indigestion and sour stomach brought on by eating or drinking certain foods and beverages

Warnings

Alergy alert

Allergy alert: Do not use if you are allergic to famotidine or other acid reducers

Do not use

- if you have trouble or pain swallowing food, vomiting with blood, or bloody or black stools. These may be signs of a serious condition. See your doctor.
- with other acid reducers

Ask a doctor before use if you have

- had heartburn over 3 months. This may be a sign of a more serious condition.
- heartburn with lightheadedness, sweating or dizziness
- chest pain or shoulder pain with shortness of breath; sweating; pain spreading to arms, neck or shoulders; or lightheadedness
- frequent chest pain
- frequent wheezing, particularly with heartburn
- unexplained weight loss
- nausea or vomiting
- stomach pain
- kidney disease

Ask a doctor or pharmacist before use if you are taking a prescription drug. Acid reducers may interact with certain prescription drugs.

Stop use and ask a doctor if

- your heartburn continues or worsens
- you need to take this product for more than 14 days

PREGNANCY OR BREAST FEEDING

If pregnant or breast-feeding, ask a healthcare professional before use.

Keep out of reach of children. In case of overdose, get medical help or contact a Poison Control Center right away (1-800-222-1222).

Directions

- adults and children 12 years and over:
- to relieve symptoms, swallow 1 tablet with a glass of water. Do not chew.
- to prevent symptoms, swallow 1 tablet with a glass of water at any time from 10 to 60 minutes before eating food or drinking beverages that cause heartburn
- do not use more than 2 tablets in 24 hours
- children under 12 years: ask a doctor

Other information

- read the directions and warnings before use
- keep the carton. It contains important information.
- store at 20º-25ºC (68º-77ºF)
- protect from moisture

Inactive ingredients

carnauba wax, corn starch, hydroxypropyl cellulose, hypromellose, magnesium stearate, microcrystalline cellulose, red iron oxide, sodium starch glycolate, talc, titanium dioxide, yellow iron oxide

Questions or comments?

call 1-800-633-1610 or visit www.zantacotc.com

Product manufactured for:
Chattem, Inc., a Sanofi Company
P.O. Box 2219
Chattanooga, TN 37409-0219
©2021 Made in India

Product repackaged and distributed by:
Lil' Drug Store Products, Inc.
9300 Earhart Lane SW, Cedar Rapids, IA 52404
1-877-507-6516 (M-F 8AM-4:30PM CST)
www.lildrugstore.com 97585C-US-04-21

PDP/Package

NEW FORMULA MAXIMUM STRENGTH
See New Warnings

Zantac

360°™

Famotidine Tablets USP 20 mg / Acid Reducer

JUST ONE TABLET

PREVENTS
& RELIEVES
HEARTBURN

DUE TO ACID
INDIGESTION

[tablet image]

Actual Size

5 Tablets

(5 Doses)

[Lil' Drug Store logo]

Zantac 360°™, Lil' Drug Store® - PDP/Package

NEW FORMULA MAXIMUM STRENGTH
See New Warnings

Zantac

360°™

Famotidine Tablets USP 20 mg / Acid Reducer

JUST ONE TABLET

PREVENTS
& RELIEVES
HEARTBURN

DUE TO ACID
INDIGESTION

[tablet image]

Actual Size

2 Tablets

(2 Doses)

[Lil' Drug Store logo]

Zantac 360°™, Travel BASIX

NEW FORMULA
See New Warnings

MAXIMUM STRENGTH

Zantac

360°™

Famotidine Tablets USP 20 mg / Acid Reducer

JUST ONE TABLET

PREVENTS
& RELIEVES
HEARTBURN

DUE TO ACID
INDIGESTION

[tablet image]

Actual Size

2 Tablets

[Travel BASIX logo]